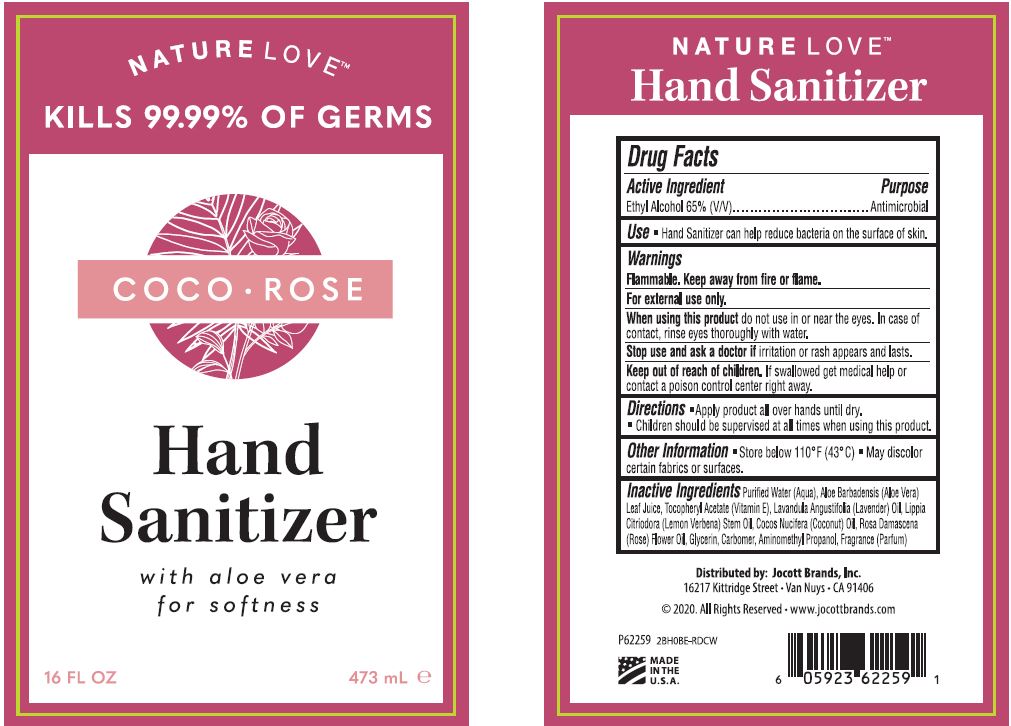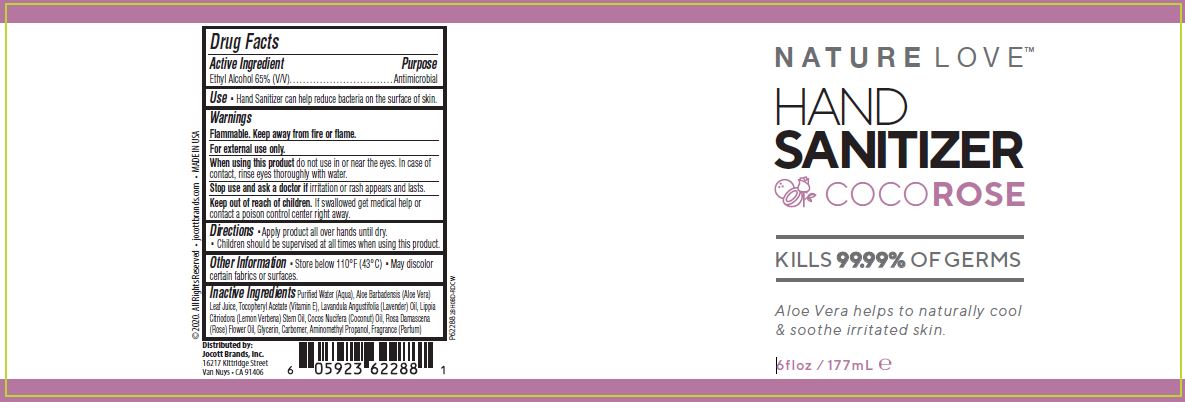 DRUG LABEL: HAND SANITIZER
NDC: 78902-112 | Form: GEL
Manufacturer: Jocott Brands, Inc.
Category: otc | Type: HUMAN OTC DRUG LABEL
Date: 20200901

ACTIVE INGREDIENTS: ALCOHOL 65 mL/100 mL
INACTIVE INGREDIENTS: WATER; ALOE VERA LEAF; .ALPHA.-TOCOPHEROL ACETATE; LAVENDER OIL; ALOYSIA CITRODORA FLOWER OIL; COCONUT OIL; ROSE OIL; GLYCERIN; CARBOMER HOMOPOLYMER, UNSPECIFIED TYPE; AMINOMETHYLPROPANOL

HAND SANITIZER GEL - COCO ROSE - 65% Ethyl Alcohol

ACTIVE INGREDIENT

ETHYL ALCOHOL 65% (V/V)

PURPOSE

ANTIMICROBIAL

USE

- HAND SANITIZER CAN HELP REDUCE BACTERIA ON THE SURFACE OF SKIN.

WARNINGS

FLAMMABLE. KEEP AWAY FROM FIRE OR FLAME.

FOR EXTERNAL USE ONLY.

WHEN USING THIS PRODUCT DO NOT USE IN OR NEAR THE EYES. IN CASE OF CONTACT, RINSE EYES THOROUGHLY WITH WATER.

STOP USE AND ASK A DOCTOR IF IRRITATION OR RASH APPEARS AND LASTS.

KEEP OUT OF REACH OF CHILDREN. IF SWALLOWED GET MEDICAL HELP OR CONTACT A POISON CONTROL CENTER RIGHT AWAY.

DIRECTIONS

- APPLY PRODUCT ALL OVER HANDS UNTIL DRY.
- CHILDREN SHOULD BE SUPERVISED AT ALL TIMES WHEN USING THIS PRODUCT.

OTHER INFORMATION

- STORE BELOW 110°F (43°C)
- MAY DISCOLOR CERTAIN FABRICS OR SURFACES

INACTIVE INGREDIENTS

Purified Water (Aqua), Aloe Barbadensis (Aloe Vera) Leaf Juice, Tocopheryl Acetate (Vitamin E), Lavandula Angustifolia (Lavender) Oil, Lippia
Citriodora (Lemon Verbena) Stem Oil, Cocos Nucifera (Coconut) Oil, Rosa Damascena (Rose) Flower Oil, Glycerin, Carbomer, Aminomethyl Propanol, Fragrance (Parfum)